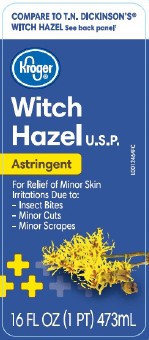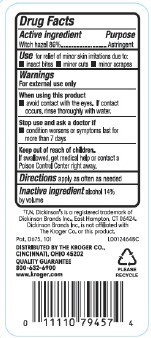 DRUG LABEL: Witch Hazel
NDC: 30142-822 | Form: LIQUID
Manufacturer: The Kroger Co.
Category: otc | Type: HUMAN OTC DRUG LABEL
Date: 20260227

ACTIVE INGREDIENTS: WITCH HAZEL 860 mg/1 mL
INACTIVE INGREDIENTS: ALCOHOL

Kroger 822.001/822AA
Witch Hazel

Active ingredient

Witch hazel 86%

Purpose

Astringent

Use

for relief of minor skin irritations due to:

- insect bites
- minor cuts
- minor scrapes

Warnings

For external use only

When using this product

avoid contact with the eyes

Stop use and ask a doctor if

- condition worsens or symptoms persist for more than 7 days

Keep out of reach of children.

If swallowed, get medical help or contact a Poison Control Center right away.

Directions

apply as often as needed

Inactive ingredient

alcohol 14% by volume

Disclaimer

†T.N. Dickinson's is a registered trademark of Dickinson Brands Inc., East Hampton, CT 06424.

Dickinson Brands Inc. is not affiliated with The Kroger Co. or this product.

Adverse reactions

Pat. D675, 101

DISTRIBUTED BY THE KROGER CO.

CINCINNATI, OH 452O2

QUALITY GUARANTEE

800-632-6900

www.kroger.com

PLEASE RECYCLE

principal display panel

COMPARE TO T.N. DICKINSON'S®WITCH HAZEL See back panel†

Kroger®

WITCH HAZEL U.S.P.

Astringent

For relief of minor skin irritations due to:

- Insect Bites
- Minor Cuts
- Minor Scrapes

16 FL OZ (1 PT) 473 mL